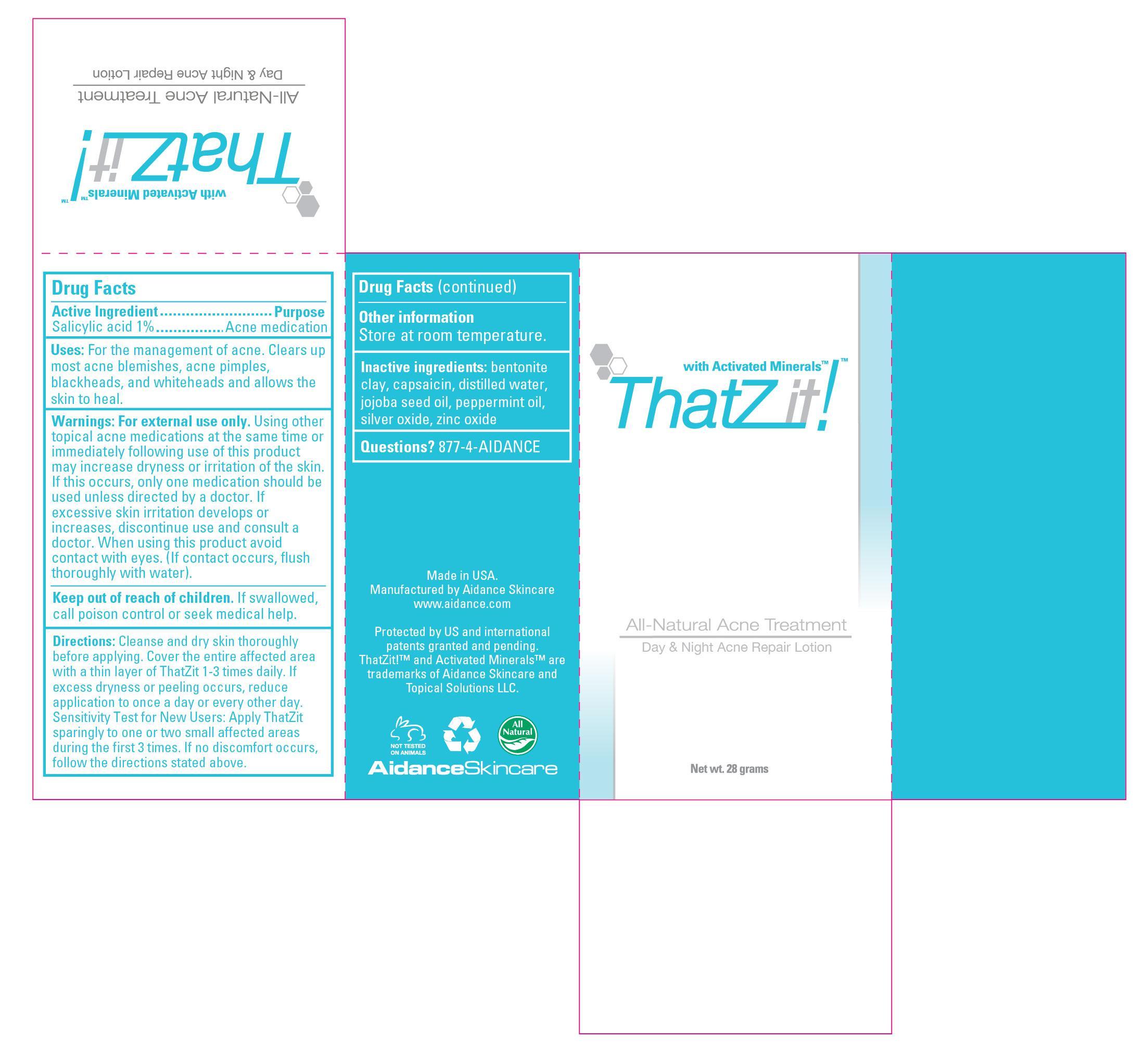 DRUG LABEL: ThatZit Acne Treatment
NDC: 24909-401 | Form: LOTION
Manufacturer: Aidance Skincare & Topical Solutions, LLC
Category: otc | Type: HUMAN OTC DRUG LABEL
Date: 20120905

ACTIVE INGREDIENTS: SALICYLIC ACID 1.0 g/100 g
INACTIVE INGREDIENTS: BENTONITE; CAPSAICIN; JOJOBA OIL; PEPPERMINT OIL; SILVER OXIDE; WATER; ZINC OXIDE

Drug Facts

Active Ingredient

Salicylic Acid 1%

Purpose

Acne Medication

Uses

For the management of acne. Clears up most acne blemishes, acne pimples, blackheads, and whiteheads and allows the skin to heal.

Warnings

For external use only. Using other topical acne medications at the same time or immediately following use of this product may increase dryness or irritation of the skin. If this occurs, only one medication should be used unless directed by a doctor. If excessive skin irritation develops or increases, discontinue use and consult a doctor. When using this product avoid contact with eyes. (If contact occurs, flush thoroughly with water).

.

Keep out of reach of children.

If swallowed, call poison control or seek medical help.

Directions

Cleanse and dry skin thoroughly before applying. Cover the entire affected area with a thin layer of ThatZit 1-3 times daily. If excess dryness or peeling occurs, reduce application to once a day or every other day. Sensitivity Test for New Users: Apply ThatZit sparingly to one or two small affected areas during the first 3 times. If no discomfort occurs, follow the directions stated above.

Other Information

Store at room temperature.

Inactive Ingredients

bentonite clay, capsaicin, distilled water, jojoba seed oil, peppermint oil, silver oxide, zinc oxide.

Questions? 877-4-AIDANCE